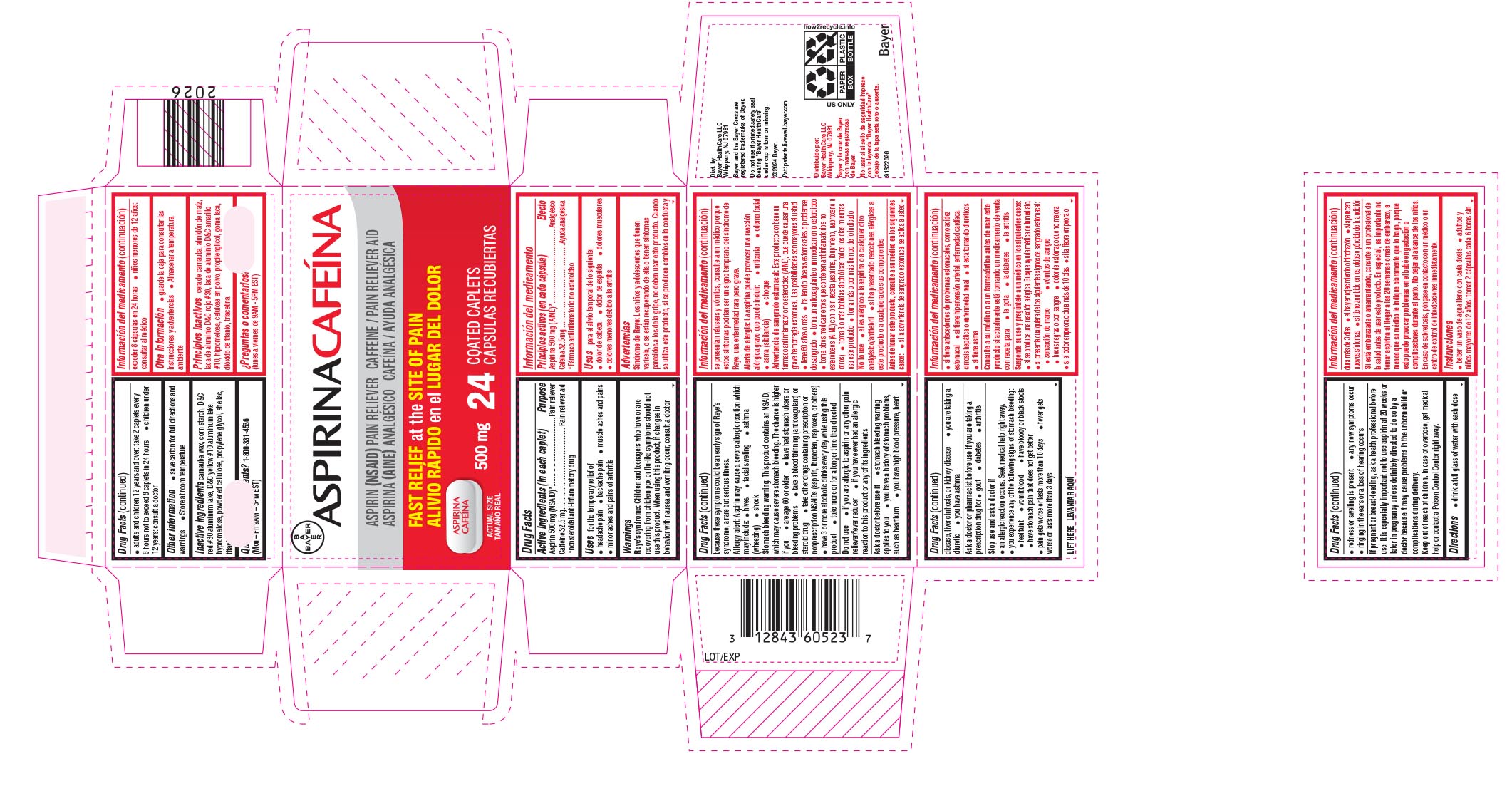 DRUG LABEL: Aspirina Cafeina
NDC: 0280-0162 | Form: TABLET
Manufacturer: Bayer HealthCare LLC.
Category: otc | Type: HUMAN OTC DRUG LABEL
Date: 20250612

ACTIVE INGREDIENTS: CAFFEINE 32.5 mg/1 1; ASPIRIN 500 mg/1 1
INACTIVE INGREDIENTS: STARCH, CORN; D&C RED NO. 30; D&C YELLOW NO. 10; HYPROMELLOSES; POWDERED CELLULOSE; PROPYLENE GLYCOL; SHELLAC; TITANIUM DIOXIDE; CARNAUBA WAX; TRIACETIN

Aspirina Cafeina UI 1600654

Drug Facts/Información del medicamento

Drug Facts

Active ingredients (in each caplet)/Principios activos (en cada cápsula)

Aspirin 500 mg (NSAID)*

Caffeine 32.5 mg

*nonsteroidal anti-inflammatory drug

Aspirina 500 mg (AINE)*

Cafeína 32.5 mg

*Fármaco antiinflamatorio no esteroideo

Purpose/Efecto

Pain Reliever

Pain reliever aid

Analgésico

Ayuda analgésica

Uses/Usos

for the temporary relief of

- headache pain
- backache pain
- muscle aches and pains
- minor aches and pains of arthritis

para el alivio temporal de lo siguiente:

- dolor de cabeza
- dolor de espalda
- dolores musculares
- dolores menores debido a la artritis

Warnings/Advertencias

Reye’s syndrome: Children and teenagers who have or are recovering from chicken pox or flu-like symptoms should not use this product. When using this product, if changes in behavior with nausea and vomiting occur, consult a doctor because these symptoms could be an early sign of Reye’s syndrome, a rare but serious illness.

Allergy alert: Aspirin may cause a severe allergic reaction which may include:

- hives
- facial swelling
- asthma (wheezing)
- shock

Stomach bleeding warning: This product contains an NSAID, which may cause severe stomach bleeding. The chance is higher if you

- are age 60 or older
- have had stomach ulcers or bleeding problems
- take a blood thinning (anticoagulant) or steroid drug
- take other drugs containing prescription or nonprescription NSAIDs (aspirin, ibuprofen, naproxen, or others)
- have 3 or more alcoholic drinks every day while using this product
- take more or for a longer time than directed

Síndrome de Reye: Los niños y adolescentes que tienen varicela, o se están recuperando de ella o tienen síntomas parecidos a los de la gripe, no deben usar este producto. Cuando se utiliza este producto, si se producen cambios en la conducta y se presentan náuseas y vómitos, consulte a un médico porque estos síntomas podrían ser un signo temprano del síndrome de Reye, una enfermedad rara pero grave.

Alerta de alergia: La aspirina puede provocar una reacción alérgica grave que puede incluir:

- urticaria
- edema facial
- asma (sibilancia)
- choque

Advertencia de sangrado estomacal: Este producto contiene un fármaco antiinflamatorio no esteroideo (AINE), que puede causar una grave hemorragia estomacal. Las posibilidades son mayores si usted

- tiene 60 años o más
- ha tenido úlceras estomacales o problemas de sangrado
- toma un anticoagulante o un medicamento esteroideo
- toma otros medicamentos que contienen antiinflamatorios no esteroideos (AINE) con o sin receta (aspirina, ibuprofeno, naproxeno u otros)
- toma 3 o más bebidas alcohólicas todos los días mientras usa este producto

Do not use/No lo use

- if you are allergic to aspirin or any other pain reliever/fever reducer
- if you have ever had an allergic reaction to this product or any of its ingredients

- si es alérgico a la aspirina o a cualquier otro analgésico/antifebril
- si ha presentado reacciones alérgicas a este producto o a cualquiera de sus componentes

Ask a doctor before use if/Antes de tomar este producto, consulte a su médico en los siguientes casos

- stomach bleeding warning applies to you
- you have a history of stomach problems, such as heartburn
- you have high blood pressure, heart disease, liver cirrhosis, or kidney disease
- you are taking a diuretic
- you have asthma

- si la advertencia de sangrado estomacal se aplica a usted
- si tiene antecedentes de problemas estomacales, como acidez estomacal
- si tiene hipertensión arterial, enfermedad cardíaca, cirrosis hepática o enfermedad renal
- si está tomando diuréticos
- si tiene asma

Ask a doctor or pharmacist before use if you are taking a prescription drug for/ Consulte a su médico o a un farmacéutico antes de usar este producto si actualmente está tomando un medicamento de venta con receta para

- gout
- diabetes
- arthritis

- la gota
- la diabetes
- la artritis

Stop use and ask a doctor if/Suspenda su uso y pregúntele a un médico en los siguientes casos

- an allergic reaction occurs. Seek medical help right away.
- you experience any of the following signs of stomach bleeding:

●feel faint ●vomit blood ●have bloody or black stools ●have stomach pain that does not get better

- pain gets worse or lasts more than 10 days
- fever gets worse or lasts more than 3 days
- redness or swelling is present
- any new symptoms occur
- ringing in the ears or a loss of hearing occurs

- si se produce una reacción alérgica. Busque ayuda médica de inmediato.
- si presenta cualquiera de los siguientes signos de sangrado estomacal:

●sensación de mareo ● vómitos de sangre ● heces negras o con sangre
●dolor de estómago que no mejora

- si el dolor empeora o dura más de 10 días
- si la fiebre empeora o dura más de 3 días
- si hay enrojecimiento o hinchazón
- si aparecen nuevos síntomas
- si tiene zumbido en los oídos o pérdida de la audición

Pregnant/Embarazada

If pregnant or breast-feeding, ask a health professional before use. It is especially important not to use aspirin at 20 weeks or later in pregnancy unless definitely directed to do so by a doctor because it may cause problems in the unborn child or complications during delivery.

Si está embarazada o amamantando,consulte a un profesional de la salud antes de usar este producto.

En especial, es importante no tomar aspirina al llegar a las 20 semanas o más de embarazo, a menos que su médico le indique claramente que lo haga, porque esto puede provocar problemas en el bebé en gestación o complicaciones durante el parto.

Keep out of reach of children. In case of overdose, get medical help or contact a Poison Control Center right away.

No dejar al alcance de los niños. En caso de sobredosis, póngase en contacto con un médico o un centro de control de intoxicaciones inmediatamente.

Directions/Instrucciones

- drink a full glass of water with each dose
- adults and children 12 years and over: take 2 caplets every 6 hours not to exceed 8 caplets in 24 hours
- children under 12 years: consult a doctor

- beber un vaso de agua lleno con cada dosis
- adultos y niños mayores de 12 años: tomar 2 cápsulas cada 6 horas sin exceder 8 cápsulas en 24 horas
- niños menores de 12 años: consultar al médico

Other Information/Otra información

- save carton for full directions and warnings
- Store at room temperature.

- guarde la caja para consultar las instrucciones y advertencias
- Almacenar a temperatura ambiente

Inactive Ingredients/Principios inactivos

carnauba wax, corn starch, D&C red #30 aluminum lake, D&C yellow #10 aluminum lake, hypromellose, powdered cellulose, propylene glycol, shellac, titanium dioxide, triacetin

cera de carnauba, almidón de maíz, laca de aluminio D&C rojo #30, laca de aluminio D&C amarillo #10, hipromelosa, celulosa en polvo, propilenglicol, goma laca, dióxido de titanio, triacetina

Questions or comments? 1-800-331-4536 (Mon-Fri 9AM - 5PM EST)

¿Preguntas o comentarios? 1-800-331-4536 (lunes a viernes de 9AM - 5PM EST)